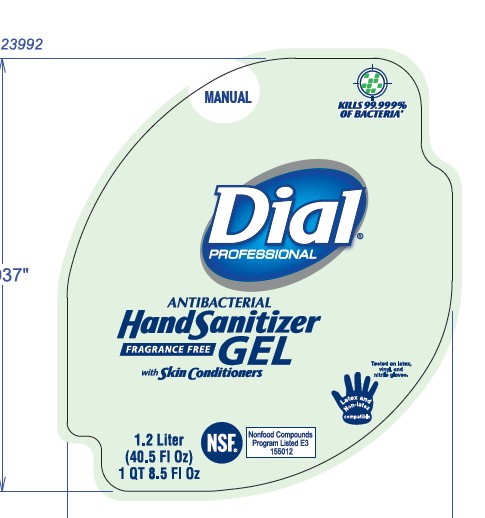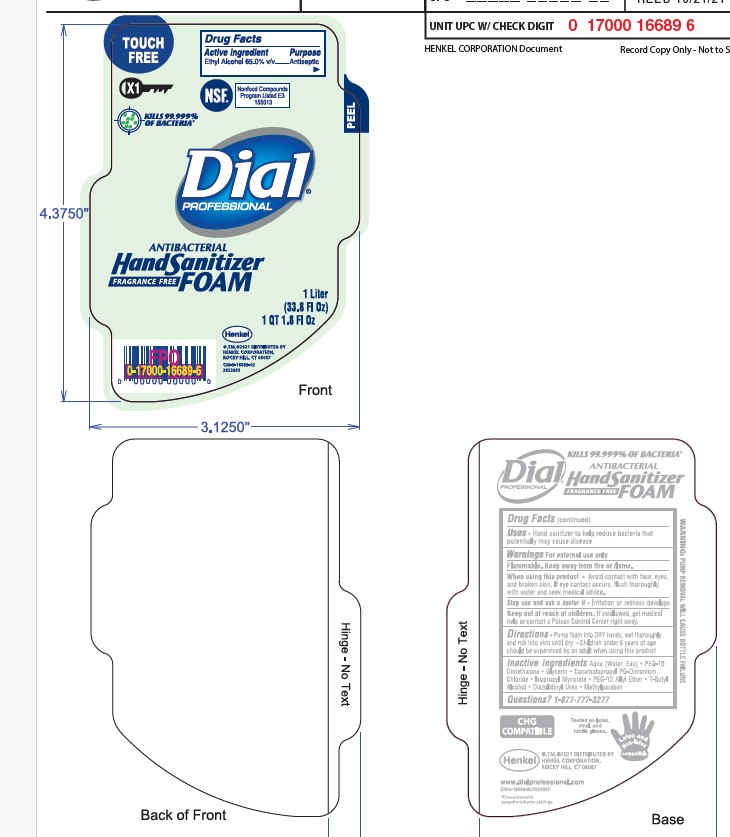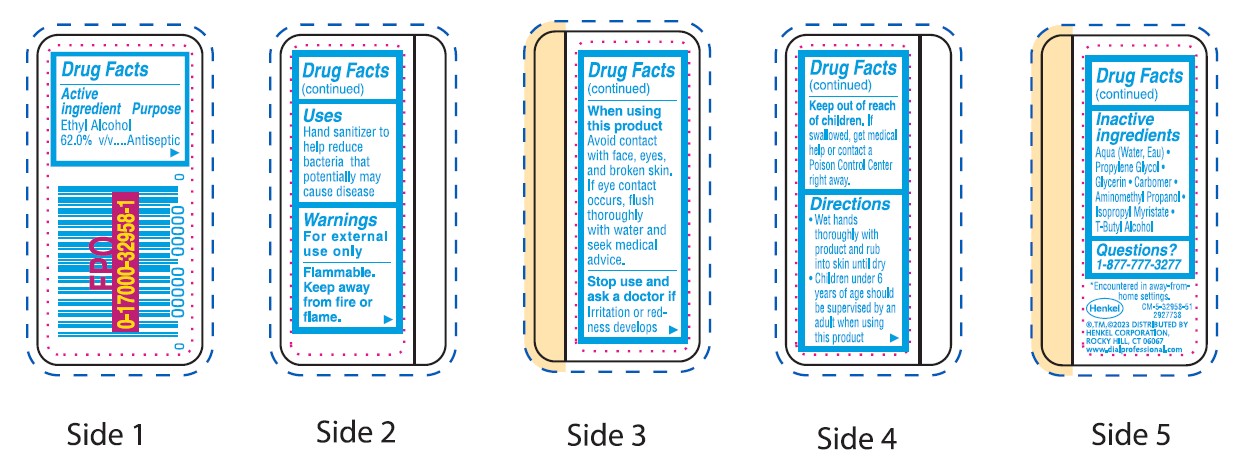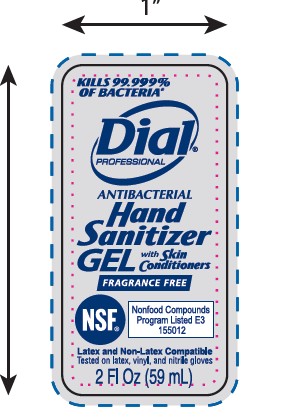 DRUG LABEL: Dial Professional Gel Sanitizer
NDC: 54340-171 | Form: GEL
Manufacturer: Henkel Corporation
Category: otc | Type: HUMAN OTC DRUG LABEL
Date: 20260227

ACTIVE INGREDIENTS: ALCOHOL 62.75 mL/100 mL
INACTIVE INGREDIENTS: WATER 33.96 mL/100 mL

Dial Professional Gel Hand Sanitizer FIT Universal Manual - Refill 3/1.2L
Dial Professional Instant Hand Sanitizer with Moisturizers - 12/7.5oz Pump
Versa™ (Formerly Eco-Smart) Direct Connect Dial Professional Hand Sanitizer Gel - Pouch Refill 6/15oz
Dial Professional Hand Sanitizer Gel FIT X1 Manual - 3/1.2L
Dial Professional Antibacterial Hand Sanitizer Gel

Dial Hand Sanitzer (Gel/Foaming)

Dial Professional Gel Hand Sanitizer

Active Ingredient: Ethyl Alcohol 62.0% v/v Purpose: Antiseptic

Inactive Ingredients: Aqua (Water, Eau) · Propylene Glycol · Glycerin · Carbomer · Aminomethyl Propanol · Isopropyl Myristate · T-Butyl Alcohol

Dial Professional Foaming Hand Sanitizer

Active Ingredient: Ethyl Alcohol 65% v/v Purpose: Antiseptic

Inactive Ingredients: Aqua (Water, Eau) · PEG-10 Dimethicone · Glycerin · Cocamidopropyl PG-Dimonium Chloride · Isopropyl Myristate · PEG-12 Allyl Ether · T-Butyl Alcohol · Diazolidinyl Urea · Methylparaben

Warnings

Warnings For external use only
Flammable. Keep away from fire or flame.

When using this product•Avoid contact with face, eyes, and broken skin. •If eye contact occurs, flush thoroughly with water and seek medical advice.ORWhen using this productavoid contact with face, eyes, and broken skin.If eye contact occurs, flush thoroughly with water and seek medical advice.
Stop use and ask a doctor if•Irritation or redness developsORStop use and ask a doctor ifirritation or redness develops
Keep out of reach of children. •If swallowed, get medical help or contact a Poison Control Center right away

DOSAGE AND ADMINISTRATION

Use(s)Hand sanitizer to help reduce bacteria thatpotentially may cause disease

INDICATIONS AND USAGE

Use(s)Hand sanitizer to help reduce bacteria thatpotentially may cause disease

Inactive Ingredients:

Aqua

PEG-10 Dimethicone

Glycerin

Cocamidopropyl PG-Dimonium Chloride

Isopropyl Myristate

PEG-12 Allyl Ether

T-Butyl Alcohol

Diazolidinyl Urea

Methylparaben